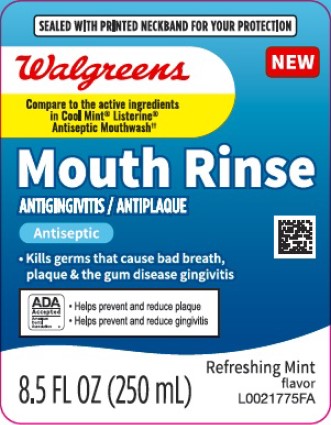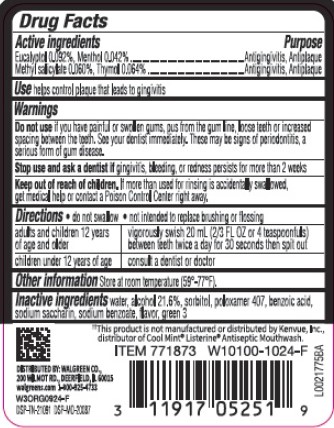 DRUG LABEL: Antispetic
NDC: 0363-0664 | Form: MOUTHWASH
Manufacturer: Walgreen Co.
Category: otc | Type: HUMAN OTC DRUG LABEL
Date: 20260212

ACTIVE INGREDIENTS: EUCALYPTOL 0.92 mg/1 mL; MENTHOL 0.42 mg/1 mL; METHYL SALICYLATE 0.6 mg/1 mL; THYMOL 0.64 mg/1 mL
INACTIVE INGREDIENTS: WATER; ALCOHOL; SORBITOL; POLOXAMER 407; BENZOIC ACID; SACCHARIN SODIUM; SODIUM BENZOATE; FD&C GREEN NO. 3

Walgreens 664.003/664AT rev 2-AU
Blue Mint Antiseptic Mouthrinse

Active Ingredients

Eucalyptol 0.092%

Menthol 0.042%

Methyl salicylate 0.060%

Thymol 0.064%

Purpose

Antigingivitis, Antiplaque

Use

helps control plaque that leads to gingivitis

Warnings

for this product

Do not use

if you have painful or swollen gums, pus from the gum line, loose teeth or increased spacing between the teeth. See your dentist immediately. These may be signs of periodontitis, a serious form of gum disease.

Stop use and ask a dentist if

gingivitis, bleeding, or redness persists for more than 2 weeks.

Keep out of reach of children.

If more than used for rinsing is accidentally swallowed, get medical help or contact a Poison Control Center right away.

Directions

- do not swallow
- not intended to replace brushing or flossing

adults and children 12 years of age and older - vigorously swish 20 mL (2/3 FL OZ or 4 teaspoonfuls) between teeth twice a day for 30 seconds then spit out

children under 12 years of age - consult a dentist or doctor

Other information

Store at room temperature (59°-77°F).

Inactive ingredients

water, alcohol 21.6%, sorbitol, poloxamer 407, benzoic acid, sodium saccharin, sodium benzoate, flavor, green 3

Disclaimer

‡This product is not manufactured or distributed by Kenvue, Inc., distributor of Cool Mint®Listerine®Antiseptic Mouthwash.

Adverse Reactions

DISTRIBUTED BY: WALGREEN CO.

200 MILMOT RD., DEERFIELD, IL 60015

walgreens.com 1-800-925-4733

DSP-TN-21091 DSP-MO-20087

Principal display panel

SEALED WITH PRINTED NECKBAND FOR YOUR PROTECTION

Walgreens

NEW

Compare to the active ingredients in Cool Mint®Listerine®Antiseptic Mouthwash‡

Mouth Rinse

ANTIGINGIVITIS/ANTIPLAQUE

Antiseptic

- Kills germs that cause bad breath, plaque & the gum disease gingivitis

ADA Accepted

American Dental Association

- Helps prevent and reduce plaque
- Helps prevent and reduce gingivitis

8.5 FL OZ. (250 mL)

Refreshing Mint flavor